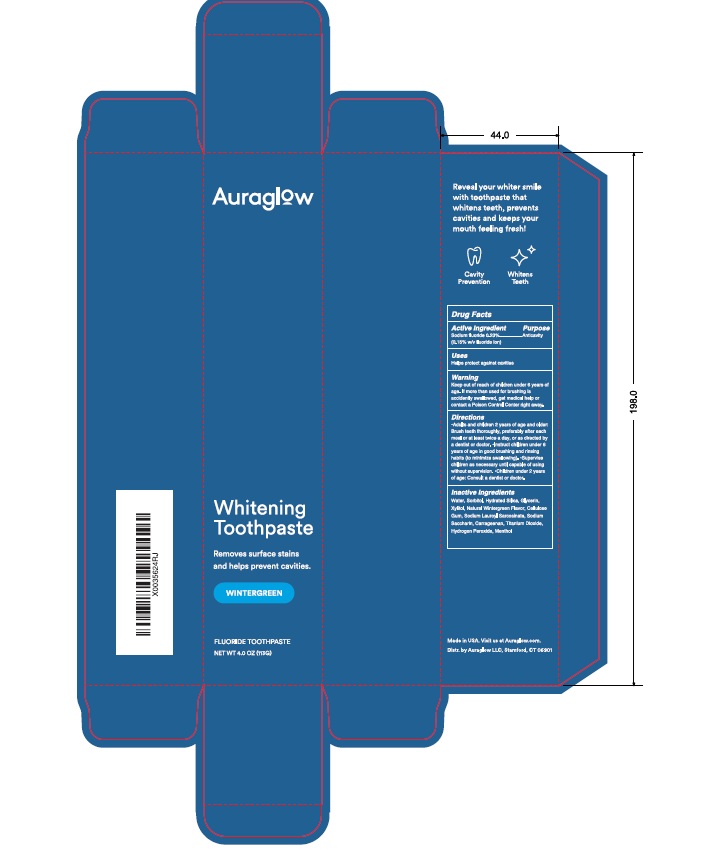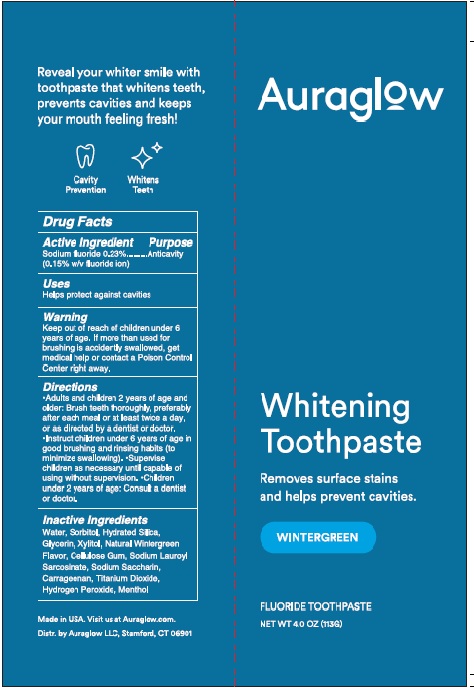 DRUG LABEL: Auraglow Whitening
NDC: 81740-003 | Form: PASTE, DENTIFRICE
Manufacturer: Auraglow LLC
Category: otc | Type: HUMAN OTC DRUG LABEL
Date: 20251022

ACTIVE INGREDIENTS: SODIUM FLUORIDE 2.3 mg/1 g
INACTIVE INGREDIENTS: WATER; SORBITOL; HYDRATED SILICA; GLYCERIN; XYLITOL; CELLULOSE GUM; SODIUM LAUROYL SARCOSINATE; SODIUM SACCHARIN; CARRAGEENAN; TITANIUM DIOXIDE; HYDROGEN PEROXIDE; MENTHOL

Auraglow Whitening Toothpaste

Drug Facts

Active ingredient

Sodium fluoride 0.23%

(0.15% w/v fluoride ion)

Purpose Anticavity

INDICATIONS AND USAGE

Use Helps protect against cavities

Warnings

Keep out of reach of children under 6 years of age.

If more than used for brushing is accidentally swallowed, get

medical help or contact a Poison Control Center right away.

Directions

• Adults and children 2 years of age and older:
Brush teeth thouroughly, preferably after each meal or
at least twice a day, or as directed by a dentist or doctor.
• Instruct children under 6 years of age in good brushing
and rinsing habits (to minimize swallowing). • Supervise
children as necessary until capable of using without supervision.

• Children under 2 years of age: Consult a dentist or doctor.

Inactive Ingredients

Water, Sorbitol, Hydrated Silica, Glycerin,

Xylitol, Natural Wintergreen Flavor, Cellulose

Gum, Sodium Lauroyl Sarcosinate, Sodium

Saccharin, Carrargeenan, Titanium Dioxide,

Hydrogen Peroxide, Menthol

Package Labeling

----------------------------------

Auraglow

Whitening

Toothpaste

Removes surface stains

and helps prevent cavities.

WINTERGREEN

FLUORIDE TOOTHPASTE

NET WT 4.0 OZ (113G)

Distr. by Auraglow LLC, Stamford, CT 06901

CARTON

TUBE

res